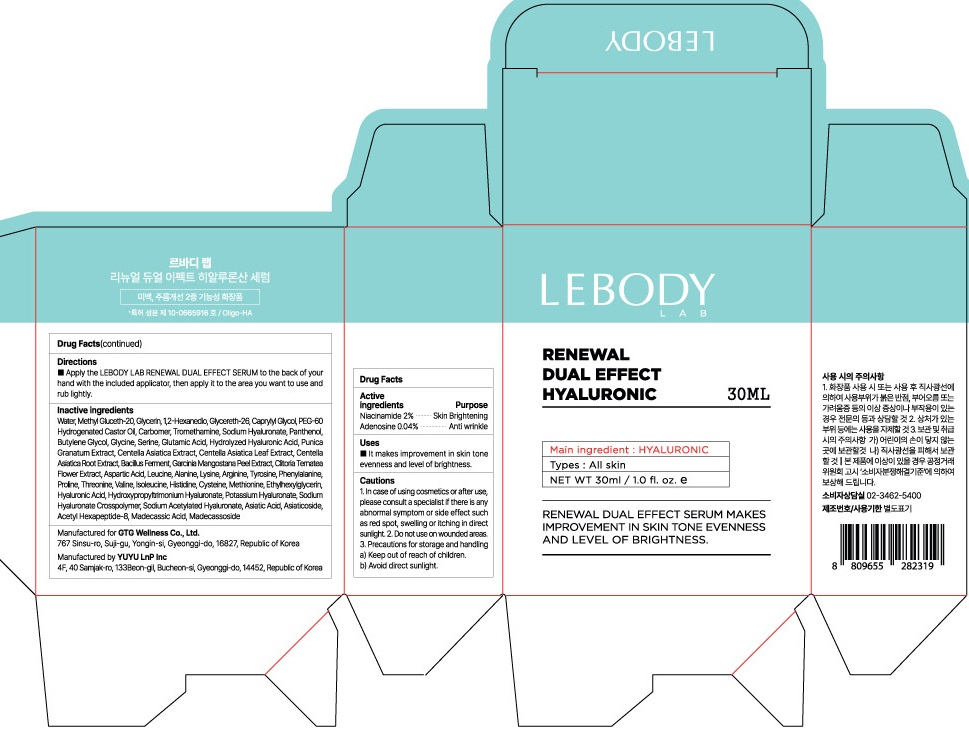 DRUG LABEL: LEBODY LAB RENEWAL DUAL EFFECT HYALURONIC SERUM
NDC: 71080-0010 | Form: LIQUID
Manufacturer: GTG Wellness Co., Ltd.
Category: otc | Type: HUMAN OTC DRUG LABEL
Date: 20230224

ACTIVE INGREDIENTS: Niacinamide 0.6 g/30 mL
INACTIVE INGREDIENTS: Water; Glycerin

ACTIVE INGREDIENTS

Niacinamide 2%

Adenosine 0.04%

INACTIVE INGREDIENTS

Water, Methyl Gluceth-20, Glycerin, 1,2-Hexanedio, Glycereth-26, Caprylyl Glycol, PEG-60 Hydrogenated Castor Oil, Carbomer, Tromethamine, Sodium Hyaluronate, Panthenol, Butylene Glycol, Glycine, Serine, Glutamic Acid, Hydrolyzed Hyaluronic Acid, Punica Granatum Extract, Centella Asiatica Extract, Centella Asiatica Leaf Extract, Centella Asiatica Root Extract, Bacillus Ferment, Garcinia Mangostana Peel Extract, Clitoria Ternatea Flower Extract, Aspartic Acid, Leucine, Alanine, Lysine, Arginine, Tyrosine, Phenylalanine, Proline, Threonine, Valine, Isoleucine, Histidine, Cysteine, Methionine, Ethylhexylglycerin, Hyaluronic Acid, Hydroxypropyltrimonium Hyaluronate, Potassium Hyaluronate, Sodium Hyaluronate Crosspolymer, Sodium Acetylated Hyaluronate, Asiatic Acid, Asiaticoside, Acetyl Hexapeptide-8, Madecassic Acid, Madecassoside

PURPOSE

Skin Brightening

Anti wrinkle

Cautions

1. In case of using cosmetics or after use, please consult a specialist if there is any abnormal symptom or side effect such as red spot, swelling or itching in direct sunlight.
2. Do not use on wounded areas.
3. Precautions for storage and handling
a) Keep out of reach of children.
b) Avoid direct sunlight.

KEEP OUT OF REACH OF CHILDREN

Uses

■ It makes improvement in skin tone evenness and level of brightness.

Directions

■ Apply the LEBODY LAB RENEWAL DUAL EFFECT SERUM to the back of your hand with the included applicator, then apply it to the area you want to use and rub lightly.